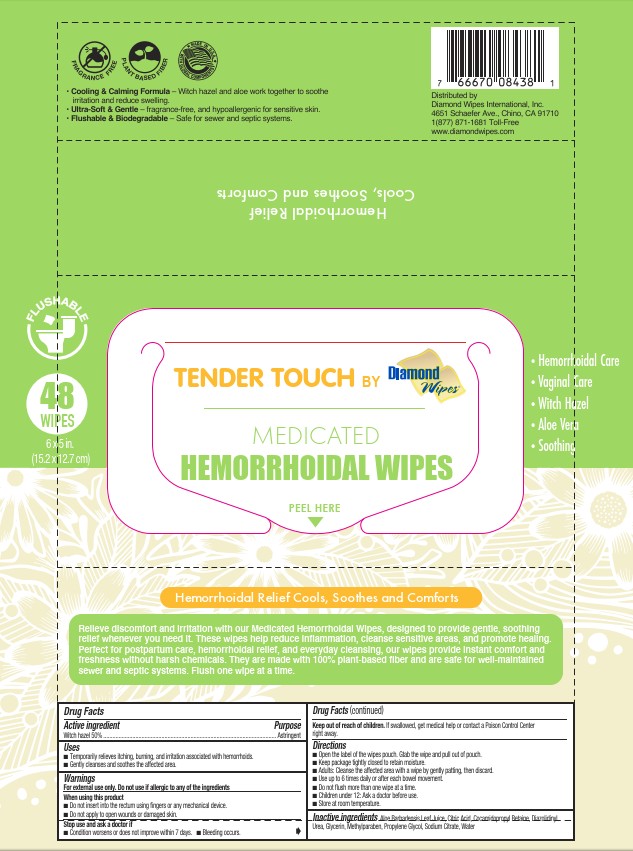 DRUG LABEL: Meicated Wipe
NDC: 64709-120 | Form: CLOTH
Manufacturer: Diamond Wipes International, Inc
Category: otc | Type: HUMAN OTC DRUG LABEL
Date: 20251124

ACTIVE INGREDIENTS: WITCH HAZEL 50 g/100 g
INACTIVE INGREDIENTS: METHYLPARABEN; CITRIC ACID; WATER; ALOE VERA LEAF; GLYCERIN; SODIUM CITRATE; COCAMIDOPROPYL BETAINE; PROPYLENE GLYCOL; DIAZOLIDINYL UREA

TENDER TOUCH BY Diamond Wipes®
MEDICATED HEMORRHOIDAL WIPES

Active ingredient

Witch hazel, 50%

Purpose

Astringent

Uses

■Temporarily relieves itching, burning, and irritation associated with hemorrhoids.

■Gently cleanses and soothes the affected area.

Warnings

For external use only. Do not use if allergic to any of the ingredients

When using this product

■ Do not insert into the rectum using fingers or any device. or applicator.

■ Do not apply to open wounds or damaged skin.

Stop use and ask a doctor if

■ Condition worsens or does not improve within 7 days.

■ Bleeding occurs.

Keep out of reach of children. If swallowed, get medical help or contact Poison Control Center right away.

Directions

■ Open the label of the wipes pouch. Gtab the wipe and pull out of pouch.

■ Keep package tightly closed to retain moisture.

■ Adults: Cleanse the affected area with a wipe by gently patting, then discard.

■ Use up to 6 times daily or after each bowel movement.

■ Do not ﬂush more than one wipe at a time.

■ Children under 12: Ask a doctor before use.

■ Store at room temperature.

Inactive ingredients

Aloe Barbadensis Leaf Juice, Citric Acid, Cocamidopropyl Betaine, Diazolidinyl Urea, Glycerin, Methylparaben, Propylene Glycol, Sodium Citrate, Water

PRINCIPAL DISPLAY PANEL

TENDER TOUCHBY Diamond Wipes®

MEDICATED HEMORRHOIDAL WIPES

PEEL HERE

Hemorrhoidal Care

Vaginal Care

Witch Hazel

Aloe Vera

Soothing

FLUSHABLE

48 WIPES

6x5in